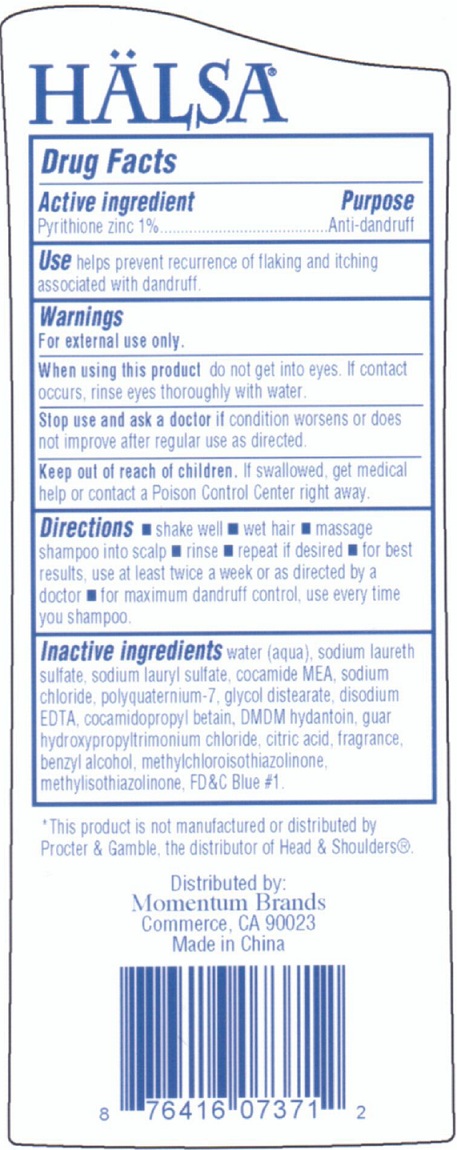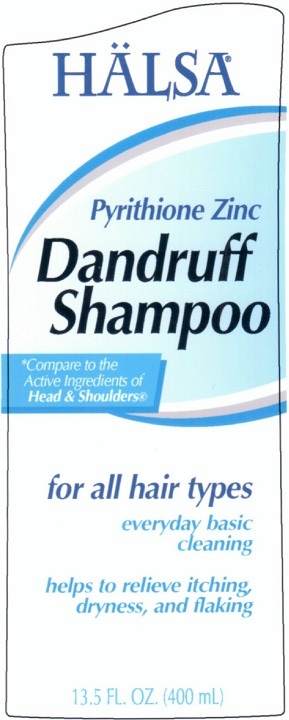 DRUG LABEL: Halsa Pyrithione Zinc Dandruff
NDC: 75884-100 | Form: SHAMPOO
Manufacturer: Momentum Brands dba 99 Cents Only Stores
Category: otc | Type: HUMAN OTC DRUG LABEL
Date: 20110110

ACTIVE INGREDIENTS: PYRITHIONE ZINC 1 mL/100 mL
INACTIVE INGREDIENTS: WATER; SODIUM LAURETH SULFATE; SODIUM LAURYL SULFATE; SODIUM CHLORIDE; GLYCOL DISTEARATE; EDETATE DISODIUM; COCAMIDOPROPYL BETAINE; CITRIC ACID MONOHYDRATE; BENZYL ALCOHOL; METHYLISOTHIAZOLINONE; FD&C BLUE NO. 1

Halsa Pyrithione Zinc Dandruff Shampoo

Active Ingredient Purpose

Pyrithione Zinc 1% Anti-dandruff

INDICATIONS AND USAGE

Use helps prevent recurrence of flaking and itching associated with dandruff.

Purpose:

Anti-dandruff

Warnings

For external use only.

When using this product do not get into eyes. If contact occurs, rinse eyes thoroughly with water.

Stop use and ask a doctor if condition worsens or does not improve after regular use as directed.

Keep out of reach of children. If swallowed, get medical help or contact a Poison Control Center right away.

Directions

Shake well

wet hair

massage shampoo into scalp

rinse

repeat if desired

for best results, use at least twice a week or as directed by a doctor

for maximum dandruff control, use every time you shampoo.

Inactive Ingredients

water (aqua), sodium laureth sulfate, sodium lauryl sulfate, cocamide MEA, sodium chloride, polyquaternium-7,

glycol distearate, disodium EDTA, cocamidopropyl betain, DMDM hydantoin guar hydropropyltrimonium chloride,

citric acid, fragrance, benzyl alcohol, methylchloroisothiazolinone, methylisothiazolinone, FD and C Blue 1

DESCRIPTION

This product is not manufactured or distributed by

Procter and Gamble, the distributor of Head and Shoulders

Distributed by:

Momentum Brands
Commerce, CA 90023
Made in China

PACKAGE LABEL

Halsa

Pyrithione Zinc

Dandruff

Shampoo

Compare to the

Active Ingredients of

Head and Shoulders

for all hair types

everyday basic

cleaning

helps to relieve itching,

dryness and light flaking

13.5 FL. OZ. (400 mL)